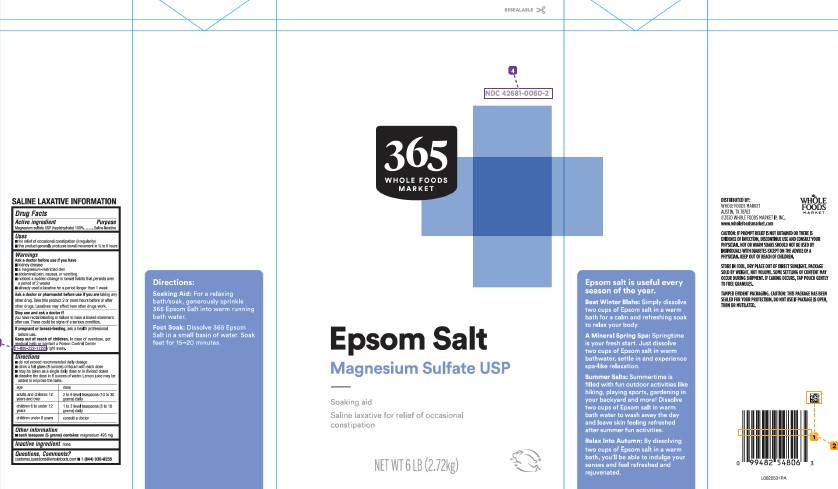 DRUG LABEL: 365 Whole Foods Market Epsom Salt
NDC: 42681-0060 | Form: GRANULE, FOR SOLUTION
Manufacturer: Whole Foods Market, Inc.
Category: otc | Type: HUMAN OTC DRUG LABEL
Date: 20260212

ACTIVE INGREDIENTS: MAGNESIUM SULFATE HEPTAHYDRATE 1 g/1 g

365 Whole Foods Market 602.002/602AA
Epsom Salt

SALINE LAXATIVE INFORMATION

for this product

Active ingredient

Magnesium sulfate USP (heptahydrate) 100%

Purpose

Saline laxative

Uses

- for relief of occasional constipation (irregularity)
- this product generally produces bowel movement in ½ to 6 hours

Warnings

for this product

Ask a doctor before use if you have

- kidney disease
- a magnesium-restricted diet
- abdominal pain, nausea, or vomiting
- noticed a sudden change in bowel habits that persists over a period of 2 weeks
- already used a laxative for a period longer than 1 week

Ask a doctor or pharmacist before use if you are

taking any other drug. Take this product 2 or more hours before or after other drugs. Laxatives may affect how other drugs work.

Stop use and ask a doctor if

you have rectal bleeding or failure to have a bowel movement after use. These could be signs of a serious condition.

If pregnant or breast-feeding,

ask a health professional before use.

Keep out of reach of children.

In case of overdose, get medical help or contact a Poison Control Center right away.

Directions

- do not exceed recommended daily dosage
- drink a full glass (8 ounces) of liquid with each dose
- may be taken as a single daily dose or in divided doses
- dissolve the dose in 8 ounces of water. Lemon juice may be added to improve the taste.

age dose

adults and children 12 years and over: 2 to 6 level teaspoons (10 to 30 grams) daily

children 6 to under 12 years: 1 to 2 level teaspoons (5 to 10 grams) daily

children under 6 years: consult a doctor

Other information

- each teaspoon (5 grams) contains: magnesium 495 mg

Inactive ingredients

None

Questions or comments?

customer.questions@wholefoods.com

- 1 (844) 936-8255

Adverse Reactions

DISTRIBUTED BY:

WHOLE FOODS MARKET

AUSTIN, TX 78703

©2020 WHOLE FOODS MARKET, INC.

www.wholefoodsmarket.com

WHOLE FOODS MARKET

Side Panel Claims

Directions:

Soaking Aid: For a relaxing bath/soak, generously sprinkle 365 Epsom Salt into warm running bath water.

Foot Soak: Dissolve 365 Epsom Salt in a small basin of water. Soak feet for 15-20 minutes.

Epsom Salt is useful every season of the year.

Beat Winter Blahs: Simply dissolve two cups of Epsom salt in a warm bath for a calm and refreshing soak to relax your body.

A Mineral Spring Spa: Springtime in your fresh start. Just dissolve two cups of Epsom salt in warm bathwater, settle in and experience spa-like relaxation.

Summer Salts: Summertime is filled with fun outdoor activities like hiking, playing sports, gardening in your backyard and more! Dissolve two cups of Epsom salt in warm bath water to wash away the day and leave skin feeling refreshed after summer fun activities.

Relax Into Autumn: By dissolving two cups of Epsom salt in a warm bath, you'll be able to indulge your senses and feel refreshed and rejuvenated.

Caution: if prompt relief is not obtained or there is evidence of infection, discontinue use and consult your physician. Hot or warm soaks should not be used by individuals with diabetes except on the advice of a physician. Keep out of reach of children.

Store in cool, dry place out of direct sunlight. Package sold by weight not volume. Some settling of content may occur during shipment. If caking occurs, tap pouch gently to free granules.

Tamper Evident Packaging. Caution: This package has been sealed for your protection. Do not use if packaging is open, torn or mutilated.

Principal Display Panel

RESEALABLE

NDC 42681-0060-2

365 WHOLE FOODS MARKET

Epsom Salt

Magnesium Sulfate USP

Soaking aid

Saline laxative for relief of occasional constipation

NET WT 6 LB (2.72 kg)